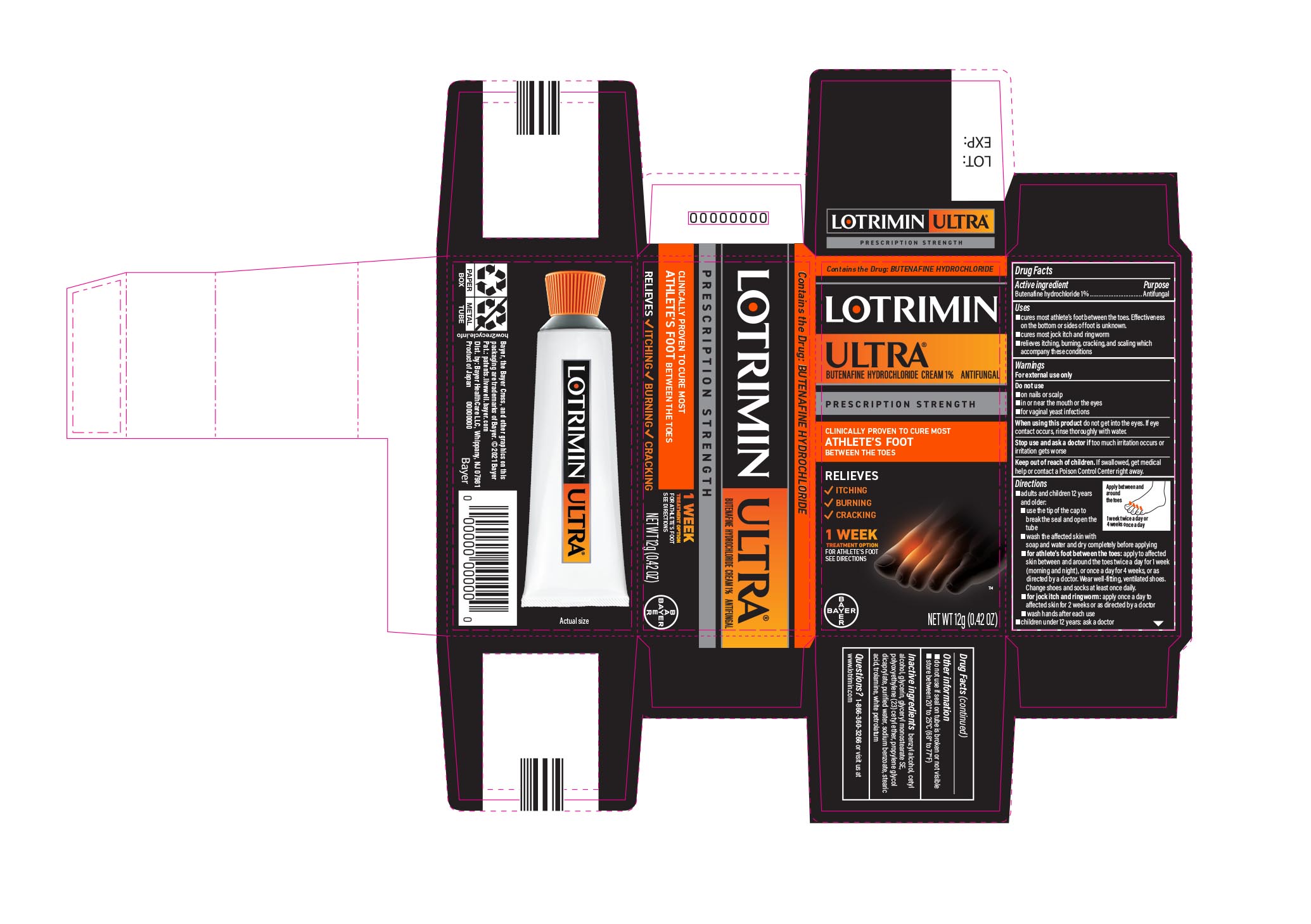 DRUG LABEL: Lotrimin Ultra
NDC: 11523-4338 | Form: CREAM
Manufacturer: Bayer Healthcare LLC.
Category: otc | Type: HUMAN OTC DRUG LABEL
Date: 20251205

ACTIVE INGREDIENTS: BUTENAFINE HYDROCHLORIDE 1 g/100 g
INACTIVE INGREDIENTS: CETYL ALCOHOL; GLYCERIN; CETETH-23; PROPYLENE GLYCOL DICAPRYLATE; WATER; SODIUM BENZOATE; STEARIC ACID; TROLAMINE; BENZYL ALCOHOL; PETROLATUM

Lotrimin Ultra®
Athlete's Foot

Drug Facts

Active ingredient

Butenafine hydrochloride 1%

Purpose

Antifungal

Uses

- cures most athlete's foot between the toes. Effectiveness on the bottom or sides of foot is unknown.
- cures most jock itch and ringworm
- relieves itching, burning, cracking, and scaling which accompany these conditions

Warnings

For external use only

Do not use

- on nails or scalp
- in or near the mouth or the eyes
- for vaginal yeast infections

When using this product do not get into the eyes. If eye contact occurs, rinse thoroughly with water.

Stop use and ask a doctor if too much irritation occurs or irritation gets worse

Keep out of reach of children. If swallowed, get medical help or contact a Poison Control Center right away.

Directions

- adults and children 12 years and older:
  - use the tip of the cap to break the seal and open the tube
  - wash the affected skin with soap and water and dry completely before applying
  - for athlete's foot between the toes: apply to affected skin between and around the toes twice a day for 1 week (morning and night), or once a day for 4 weeks, or as directed by a doctor. Wear well-fitting, ventilated shoes. Change shoes and socks at least once daily.
  - for jock itch and ringworm: apply once a day to affected skin for 2 weeks or as directed by a doctor
  - wash hands after each use
- children under 12 years: ask a doctor

Other information

- do not use if seal on tube is broken or not visible
- store between 20° to 25°C (68° to 77°F)

Inactive ingredients

benzyl alcohol, cetyl alcohol, glycerin, glyceryl monostearate SE, polyoxyethylene (23) cetyl ether, propylene glycol dicaprylate, purified water, sodium benzoate, stearic acid, trolamine, white petrolatum

Distributed by Bayer HealthCare LLC, Whippany, NJ 07981

PRINCIPAL DISPLAY PANEL - 12 g Tube Carton

LOTRIMIN ULTRA ®

butenafine hydrochloride cream 1%
ANTIFUNGAL
NET WT 12g (0.42 OZ)